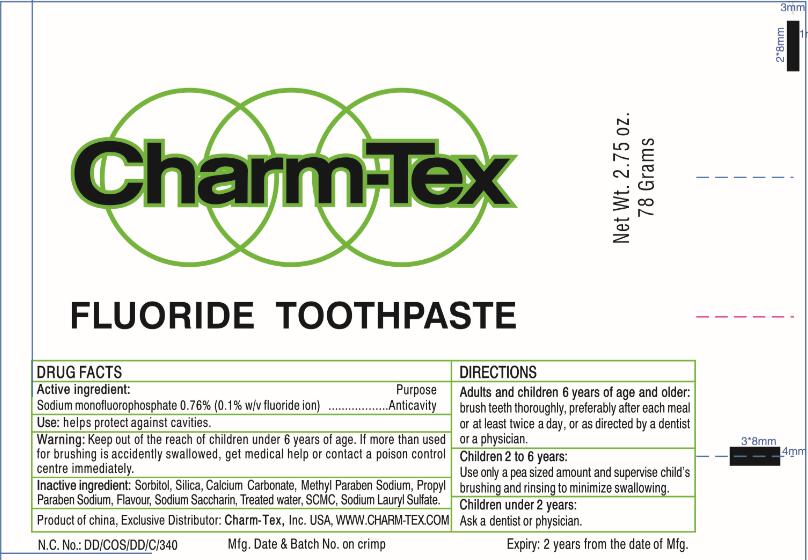 DRUG LABEL: Charm Tex Fluoride
NDC: 73343-003 | Form: PASTE
Manufacturer: Yangzhou Tracey Daily Chemical Plastic Co., Ltd.
Category: otc | Type: HUMAN OTC DRUG LABEL
Date: 20191014

ACTIVE INGREDIENTS: SODIUM MONOFLUOROPHOSPHATE 0.76 g/100 g
INACTIVE INGREDIENTS: SORBITOL; SILICA DIMETHYL SILYLATE; CALCIUM CARBONATE; METHYLPARABEN; PROPYLPARABEN SODIUM; SACCHARIN SODIUM; WATER; CARBOXYMETHYLCELLULOSE SODIUM; SODIUM LAURYL SULFATE

FLUORIDE TOOTHPASTE 73343-003

Active Ingredient

Sodium Fluoride 0.76%(0.1%w/v fluoride ion)

Purpose

Anticavity

Use

helps protect against cavities

Warning

Keep out of reach of children under 6 years of age.
If more than used for brushing is accidently swallowed get medical help or contact a poison control center immediately.

Directions

Adults and children 6 years of age and older:brush teeth thoroughly, preferably after each meal or at least twice a day,
or as directed by a dentist or a physician.
Children 2 to 6:Use only a pea sized amount and supervise child’s brushing and rinsing to minimize swallowing.
Children under 2:Ask dentist or physician

Inactive Ingredients

Sorbitol, Silica, Methyl Paraben Sodium, Propyl Paraben Sodium, Sodium Saccharin, Flavour, Treated Water, SCMC,
Sodium Lauryl Sulfate

Keep out of reach of children under 6 years of age